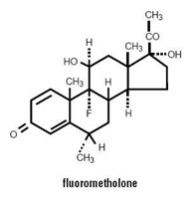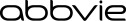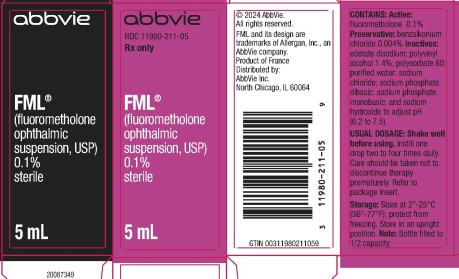 DRUG LABEL: FML
NDC: 11980-211 | Form: SUSPENSION/ DROPS
Manufacturer: Allergan, Inc.
Category: prescription | Type: HUMAN PRESCRIPTION DRUG LABEL
Date: 20231201

ACTIVE INGREDIENTS: FLUOROMETHOLONE 1 mg/1 mL
INACTIVE INGREDIENTS: BENZALKONIUM CHLORIDE; EDETATE DISODIUM; POLYSORBATE 80; POLYVINYL ALCOHOL, UNSPECIFIED; WATER; SODIUM CHLORIDE; SODIUM PHOSPHATE, DIBASIC, UNSPECIFIED FORM; SODIUM PHOSPHATE, MONOBASIC, UNSPECIFIED FORM; SODIUM HYDROXIDE

FML®
(fluorometholone ophthalmic suspension, USP) 0.1%
sterile

DESCRIPTION

FML® (fluorometholone ophthalmic suspension, USP) 0.1% is a sterile, topical anti-inflammatory agent for ophthalmic use.

Chemical Name

Fluorometholone: 9-Fluoro-11β,17-dihydroxy-6α-methylpregna-1,4-diene-3,20-dione.

Structural Formula

Contains

Active: fluorometholone 0.1%. Preservative: benzalkonium chloride 0.004%. Inactives: edetate disodium; polysorbate 80; polyvinyl alcohol 1.4%; purified water; sodium chloride; sodium phosphate, dibasic; sodium phosphate, monobasic; and sodium hydroxide to adjust pH. FML® suspension is formulated with a pH from 6.2 to 7.5. It has an osmolality range of 290-350 mOsm/kg.

CLINICAL PHARMACOLOGY

Corticosteroids inhibit the inflammatory response to a variety of inciting agents and probably delay or slow healing. They inhibit the edema, fibrin deposition, capillary dilation, leukocyte migration, capillary proliferation, fibroblast proliferation, deposition of collagen, and scar formation associated with inflammation.

There is no generally accepted explanation for the mechanism of action of ocular corticosteroids. However, corticosteroids are thought to act by the induction of phospholipase A2 inhibitory proteins, collectively called lipocortins. It is postulated that these proteins control the biosynthesis of potent mediators of inflammation such as prostaglandins and leukotrienes by inhibiting the release of their common precursor, arachidonic acid. Arachidonic acid is released from membrane phospholipids by phospholipase A2.

Corticosteroids are capable of producing a rise in intraocular pressure. In clinical studies of documented steroid-responders, fluorometholone demonstrated a significantly longer average time to produce a rise in intraocular pressure than dexamethasone phosphate; however, in a small percentage of individuals, a significant rise in intraocular pressure occurred within one week. The ultimate magnitude of the rise was equivalent for both drugs.

INDICATIONS AND USAGE

FML® suspension is indicated for the treatment of corticosteroid-responsive inflammation of the palpebral and bulbar conjunctiva, cornea and anterior segment of the globe.

CONTRAINDICATIONS

FML® suspension is contraindicated in most viral diseases of the cornea and conjunctiva, including epithelial herpes simplex keratitis (dendritic keratitis), vaccinia, and varicella, and also in mycobacterial infection of the eye, and fungal diseases of ocular structures.

FML® suspension is also contraindicated in individuals with known or suspected hypersensitivity to any of the ingredients of this preparation and to other corticosteroids.

WARNINGS

Prolonged use of corticosteroids may increase intraocular pressure in susceptible individuals, resulting in glaucoma with damage to the optic nerve, defects in visual acuity and fields of vision, and in posterior subcapsular cataract formation. Prolonged use may also suppress the host immune response and thus increase the hazard of secondary ocular infections.

Various ocular diseases and long-term use of topical corticosteroids have been known to cause corneal and scleral thinning. Use of topical corticosteroids in the presence of thin corneal or scleral tissue may lead to perforation.

Acute purulent infections of the eye may be masked or activity enhanced by the presence of corticosteroid medication.

If this product is used for 10 days or longer, intraocular pressure should be routinely monitored even though it may be difficult in children and uncooperative patients. Steroids should be used with caution in the presence of glaucoma. Intraocular pressure should be checked frequently.

The use of steroids after cataract surgery may delay healing and increase the incidence of bleb formation.

Use of ocular steroids may prolong the course and may exacerbate the severity of many viral infections of the eye (including herpes simplex). Employment of a corticosteroid medication in the treatment of patients with a history of herpes simplex requires great caution; frequent slit lamp microscopy is recommended.

PRECAUTIONS

General

The initial prescription and renewal of the medication order beyond 20 milliliters of FML® suspension should be made by a physician only after examination of the patient with the aid of magnification, such as slit lamp biomicroscopy and, where appropriate, fluorescein staining. If signs and symptoms fail to improve after two days, the patient should be re-evaluated.

As fungal infections of the cornea are particularly prone to develop coincidentally with long-term local corticosteroid applications, fungal invasion should be suspected in any persistent corneal ulceration where a corticosteroid has been used or is in use. Fungal cultures should be taken when appropriate.

If this product is used for 10 days or longer, intraocular pressure should be monitored (see WARNINGS).

Information for Patients

If inflammation or pain persists longer than 48 hours or becomes aggravated, the patient should be advised to discontinue use of the medication and consult a physician.

This product is sterile when packaged. To prevent contamination, care should be taken to avoid touching the bottle tip to eyelids or to any other surface. The use of this bottle by more than one person may spread infection. Keep bottle tightly closed when not in use. Keep out of the reach of children.

The preservative in FML® suspension, benzalkonium chloride, may be absorbed by soft contact lenses. Patients wearing soft contact lenses should be instructed to wait at least 15 minutes after instilling FML® suspension to insert soft contact lenses.

Carcinogenesis, Mutagenesis, Impairment of Fertility

No studies have been conducted in animals or in humans to evaluate the possibility of these effects with fluorometholone.

Pregnancy

Teratogenic effects

Fluorometholone has been shown to be embryocidal and teratogenic in rabbits when administered at low multiples of the human ocular dose. Fluorometholone was applied ocularly to rabbits daily on days 6-18 of gestation, and dose-related fetal loss and fetal abnormalities including cleft palate, deformed rib cage, anomalous limbs and neural abnormalities such as encephalocele, craniorachischisis, and spina bifida were observed. There are no adequate and well-controlled studies of fluorometholone in pregnant women, and it is not known whether fluorometholone can cause fetal harm when administered to a pregnant woman. Fluorometholone should be used during pregnancy only if the potential benefit justifies the potential risk to the fetus.

Nursing Mothers

It is not known whether topical ophthalmic administration of corticosteroids could result in sufficient systemic absorption to produce detectable quantities in human milk. Systemically-administered corticosteroids appear in human milk and could suppress growth, interfere with endogenous corticosteroid production, or cause other untoward effects. Because of the potential for serious adverse reactions in nursing infants from fluorometholone, a decision should be made whether to discontinue nursing or to discontinue the drug, taking into account the importance of the drug to the mother.

Pediatric Use

Safety and effectiveness in infants below the age of two years have not been established.

Geriatric Use

No overall differences in safety or effectiveness have been observed between elderly and younger patients.

ADVERSE REACTIONS

Adverse reactions include, in decreasing order of frequency, elevation of intraocular pressure (IOP) with possible development of glaucoma and infrequent optic nerve damage, posterior subcapsular cataract formation, and delayed wound healing.

Although systemic effects are extremely uncommon, there have been rare occurrences of systemic hypercorticoidism after use of topical dermatologic steroids applied to the skin.

Corticosteroid-containing preparations have also been reported to cause acute anterior uveitis and perforation of the globe. Keratitis, conjunctivitis, corneal ulcers, mydriasis, conjunctival hyperemia, loss of accommodation and ptosis have occasionally been reported following local use of corticosteroids.

The development of secondary ocular infection (bacterial, fungal and viral) has occurred. Fungal and viral infections of the cornea are particularly prone to develop coincidentally with long-term applications of steroids. The possibility of fungal invasion should be considered in any persistent corneal ulceration where steroid treatment has been used (see WARNINGS).

Transient burning and stinging upon instillation and other minor symptoms of ocular irritation have been reported with the use of FML® suspension. Other adverse events reported with the use of fluorometholone include: allergic reactions; foreign body sensation; erythema of eyelid; eyelid edema/eye swelling; eye discharge; eye pain; eye pruritus; lacrimation increased; rash; taste perversion; visual disturbance (blurry vision); and visual field defect.

DOSAGE AND ADMINISTRATION

Shake well before using. Instill one drop into the conjunctival sac two to four times daily. During the initial 24 to 48 hours, the dosing frequency may be increased to one application every four hours. Care should be taken not to discontinue therapy prematurely.

If signs and symptoms fail to improve after two days, the patient should be re-evaluated (see PRECAUTIONS).

The dosing of FML® suspension may be reduced, but care should be taken not to discontinue therapy prematurely. In chronic conditions, withdrawal of treatment should be carried out by gradually decreasing the frequency of applications.

HOW SUPPLIED

FML® (fluorometholone ophthalmic suspension, USP) 0.1% is supplied sterile in opaque white LDPE plastic bottles with white high impact polystyrene (HIPS) caps as follows:

5 mL in 10 mL bottle NDC 11980-211-05

10 mL in 15 mL bottle NDC 11980-211-10

Storage: Store at 2°-25°C (36°-77°F); protect from freezing. Store in an upright position.

Revised: 12/2023

Distributed by:
AbbVie Inc.
North Chicago, IL 60064

© 2024 AbbVie. All rights reserved.

FML and its design are trademarks of Allergan, Inc., an AbbVie company.

v2.0USPI211

PRINCIPAL DISPLAY PANEL

NDC 11980-211-05
Rx Only
FML®
(fluorometholone
ophthalmic
suspension, USP)
0.1%
sterile
5 mL
abbvie